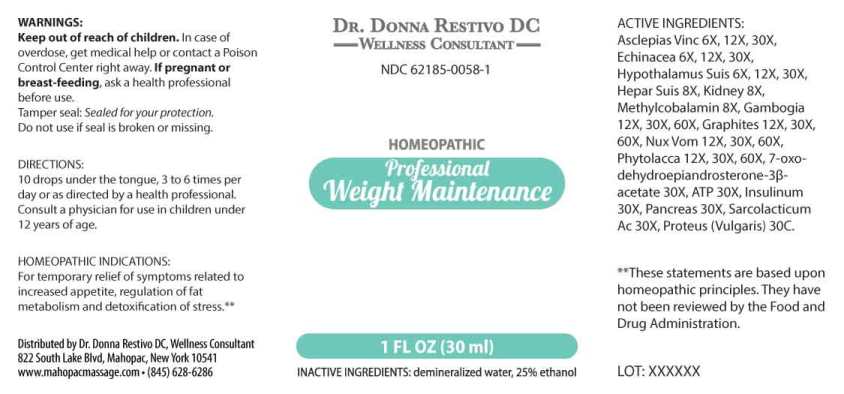 DRUG LABEL: Professional Weight Maintenance
NDC: 62185-0058 | Form: LIQUID
Manufacturer: Dr. Donna Restivo DC
Category: homeopathic | Type: HUMAN OTC DRUG LABEL
Date: 20240118

ACTIVE INGREDIENTS: CYNANCHUM VINCETOXICUM ROOT 6 [hp_X]/1 mL; ECHINACEA ANGUSTIFOLIA WHOLE 6 [hp_X]/1 mL; SUS SCROFA HYPOTHALAMUS 6 [hp_X]/1 mL; PORK LIVER 8 [hp_X]/1 mL; PORK KIDNEY 8 [hp_X]/1 mL; METHYLCOBALAMIN 8 [hp_X]/1 mL; GAMBOGE 12 [hp_X]/1 mL; GRAPHITE 12 [hp_X]/1 mL; STRYCHNOS NUX-VOMICA SEED 12 [hp_X]/1 mL; PHYTOLACCA AMERICANA ROOT 12 [hp_X]/1 mL; 7-OXODEHYDROEPIANDROSTERONE 3-ACETATE 30 [hp_X]/1 mL; ADENOSINE TRIPHOSPHATE DISODIUM 30 [hp_X]/1 mL; INSULIN PORK 30 [hp_X]/1 mL; SUS SCROFA PANCREAS 30 [hp_X]/1 mL; LACTIC ACID, L- 30 [hp_X]/1 mL; PROTEUS VULGARIS 30 [hp_C]/1 mL
INACTIVE INGREDIENTS: WATER; ALCOHOL

DRUG FACTS:

ACTIVE INGREDIENTS:

Asclepias Vincetoxicum 6X, 12X, 30X, Echinacea (Angustifolia) 6X, 12X, 30X, Hypothalamus Suis 6X, 12X, 30X, Hepar Suis 8X, Kidney (Suis) 8X, Methylcobalamin 8X, Gambogia 12X, 30X, 60X, Graphites 12X, 30X, 60X, Nux Vomica 12X, 30X, 60X, Phytolacca Decandra 12X, 30X, 60X, 7-Oxo-Dehydroepiandrosterone-3-Acetate 30X, Adenosinum Triphosphoricum Dinatrum 30X, Insulinum (Suis) 30X, Sarcolacticum Acidum 30X, Proteus (Vulgaris) 30C.

HOMEOPATHIC INDICATIONS:

For temporary relief of symptoms related to increased appetite, regulation of fat metabolism and detoxification of stress.**

**These statements are based upon homeopathic principles. They have not been reviewed by the Food and Drug Administration.

WARNINGS:

Keep out of reach of children. In case of overdose, get medical help or contact a Poison Control Center right away.

If pregnant or breast-feeding, ask a health professional before use.

Tamper seal: Sealed for your protection.

Do not use if seal is broken or missing.

Keep out of reach of children. In case of overdose, get medical help or contact a Poison Control Center right away.

DIRECTIONS:

10 drops under the tongue, 3 to 6 times per day or as directed by a health professional. Consult a physician for use in children under 12 years of age.

HOMEOPATHIC INDICATIONS:

For temporary relief of symptoms related to increased appetite, regulation of fat metabolism and detoxification of stress.**

**These statements are based upon homeopathic principles. They have not been reviewed by the Food and Drug Administration.

INACTIVE INGREDIENTS:

demineralized water, 25% ethanol

QUESTIONS:

Distributed by Dr. Donna Restivo DC, Wellness Consultant

822 South Lake Blvd, Mahopac, New York 10541

www.mahopacmassage.com (845)628-6286

PACKAGE LABEL DISPLAY:

DR. DONNA RESTIVO DC

WELLNESS CONSULTANT

NDC 62185-0058-1

HOMEOPATHIC

Professional

Weight Maintenance

1 FL OZ (30 ml)